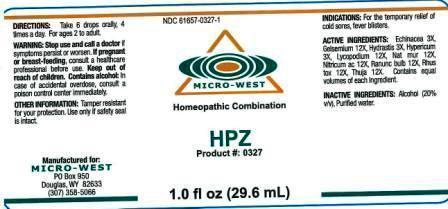 DRUG LABEL: HPZ
NDC: 61657-0327 | Form: LIQUID
Manufacturer: White Manufacturing Inc. DBA Micro-West
Category: homeopathic | Type: HUMAN OTC DRUG LABEL
Date: 20140711

ACTIVE INGREDIENTS: ST. JOHN'S WORT 3 [hp_X]/30 mL; LYCOPODIUM CLAVATUM SPORE 12 [hp_X]/30 mL; SODIUM CHLORIDE 12 [hp_X]/30 mL; THUJA OCCIDENTALIS LEAF 12 [hp_X]/30 mL; NITRIC ACID 12 [hp_X]/30 mL; GELSEMIUM SEMPERVIRENS ROOT 12 [hp_X]/30 mL; TOXICODENDRON PUBESCENS LEAF 12 [hp_X]/30 mL; ECHINACEA PURPUREA 3 [hp_X]/30 mL; GOLDENSEAL 3 [hp_X]/30 mL
INACTIVE INGREDIENTS: ALCOHOL

Drug Facts

ACTIVE INGREDIENTS

Echinacea 3X

Gelsemium 12X

Hydrastis 3X

Hypericum 3X

Lycopodium 12X

Nat mur 12X

Nitricum ac 12X

Ramunc bulb 12X

Rhus Tox 12X

Thuja 12X

KEEP OUT OF REACH OF CHILDREN

PURPOSE

FOR THE TEMPORARY RELIEF OF COLD SORES,

FEVER BLISTERS

WARNING

WARNINGS: STOP USE AND CALL A DOCTOR if symptoms persist or worsen. IF PREGNANT OR BREAST FEEDING, consult a healthcare professional before use. CONTAINS ALCOHOL: in case of accidental overdose, consult a poison control center immediately.

OTHER SAFETY INFORMATION

OTHER INFORMATION: Tamper resistant for your protection. Use only if safety seal is intact.

DIRECTIONS

DIRECTIONS: Take 6 drops orally, 4 times a day. For ages 2 to adult

INACTIVE INGREDIENTS

Alcohol 20% v/v

Purified water

INDICATIONS

INDICATIONS: For the temporary relief of cold sores, fever blisters

MANUFACTURE

MANUFACTURED FOR:

MICRO-WEST

P. O. BOX 950

DOUGLAS, WY 82633

1307-358-5066